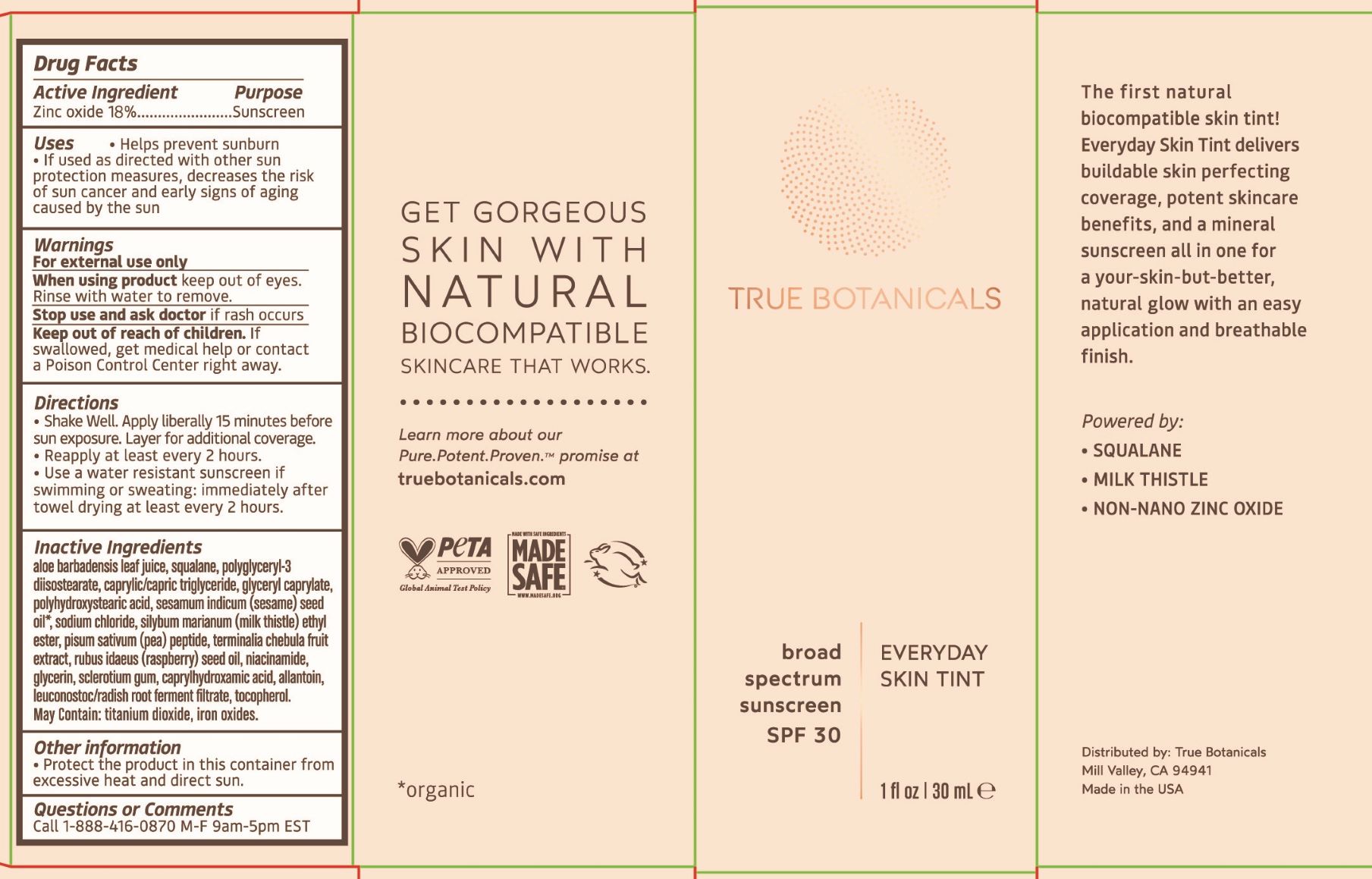 DRUG LABEL: Sunscreen
NDC: 82516-202 | Form: LOTION
Manufacturer: True Botanicals
Category: otc | Type: HUMAN OTC DRUG LABEL
Date: 20251008

ACTIVE INGREDIENTS: ZINC OXIDE 18 g/100 g
INACTIVE INGREDIENTS: WATER

True Botanicals Everyday Skin Tint - All shades

Active Ingredient

Zinc Oxide 18%

Purpose

Sunscreen

Uses

- Helps prevent sunburn

- If used as directed with other sun protection measures, decreases the risk of sun cancer and early signs of aging caused by the sun

Warnings

For external use only

When using product

keep out of eyes.
Rinse with water to remove.

Stop use and ask doctor

if rash occurs

Keep out of reach of children

If swallowed, get medical help or contact a Poison Control Center right away.

Directions

- Shake Well. Apply lierally 15 minutes before sun exposure. Layer for additional coverage.

- Reapply at least every 2 hours.

- Use a water repellant sunscreen if swimming or sweating: immediately after towel drying at least every 2 hours.

Inactive Ingredients

aloe barbadensis leaf juice, squalane, polyglyceryl-3
diisostearate, caprylic/capric triglyceride, glyceryl caprylate,
polyhydroxystearic acid, sesamum indicum (sesame) seed
oil, sodium chloride, silybum marianum (milk thistle) ethyl
ester, pisum sativum (pea) peptide, terminalia chebula fruit
extract, rubus idaeus (raspberry) seed oil, niacinamide,
glycerin, sclerotium gum, caprylhydroxamic acid, allantoin,
leuconostoc/radish root ferment filtrate, tocopherol.
May Contain: titanium dioxide, iron oxides

Other information

Protect the product in this container from excessive heat and direct sun.

Questions or Comments

Call 1-888-416-0870 M-F 9am-5pm EST